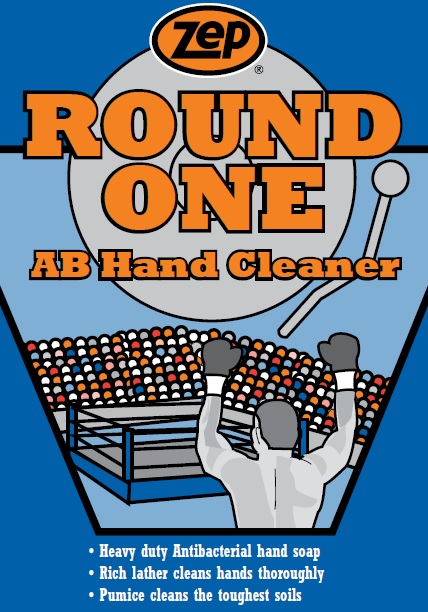 DRUG LABEL: ZEP ROUND ONE AB
NDC: 66949-129 | Form: LIQUID
Manufacturer: Zep Inc.
Category: otc | Type: HUMAN OTC DRUG LABEL
Date: 20251226

ACTIVE INGREDIENTS: CHLOROXYLENOL 0.4 g/100 mL
INACTIVE INGREDIENTS: METHACRYLIC ACID - ETHYL ACRYLATE COPOLYMER (1:1) TYPE A; C11-13 PARETH-6; TITANIUM DIOXIDE; PALMITOSTEARIC ACID; METHYLISOTHIAZOLINONE; ATTAPULGITE; WATER; SODIUM C14-16 OLEFIN SULFONATE; PUMICE; PEG-75 LANOLIN; METHYLCHLOROISOTHIAZOLINONE; GLUTARAL; COCAMIDOPROPYL HYDROXYSULTAINE; DIPOTASSIUM 4',5'-DIBROMOFLUORESCEIN; FD&C YELLOW NO. 5; STEARIC ACID

66949-129 / 3094 Round One AB

Active Ingredient

Chloroxylenol 0.4%

Purpose

Antiseptic Handwash

Uses

Hand washing to decrease bacteria on skin

Warnings

For external use only.

Do not use in or around the eyes.

When using this product

- If eye contact occurs, rinse promptly and thoroughly with water.
- Do not swallow.
- If swallowed, do not induce vomiting and if individual is conscious, give large quantities of water to drink and consult a physician immediately.

Stop use and ask a doctor if skin irritation or redness persists for more than 72 hours.

Keep out of reach of children except under adult supervision.

Directions

- Wet hands with water.
- Place hands under dispenser and apply liquid soap.
- Massage soap into hands and wrists, emphasizing back of hands, knuckles, and cuticles.
- Rinse hands thoroughly and dry.

Other information

- Do not freeze.
- Dispose in accordance with all applicable federal, state and local regulations.

Inactive ingredients

Water, Sodium C14-16 Olefin Sulfonate, Pumice, Cocamidopropyl Hydroxysultaine, Stearic Acid, Methacrylic Acid Copolymer, Attapulgite, C11-13 Pareth-6, PEG-75 Lanolin, Methylchloroisothiazolinone, Methylisothiazolinone, Fragrance, Glutaral, Titanium Dioxide, Palmitostearic Acid, Orange 7, Yellow 5

Questions or comments?

Call 1-877-I-BUY-ZEP (1-877-428-9937)